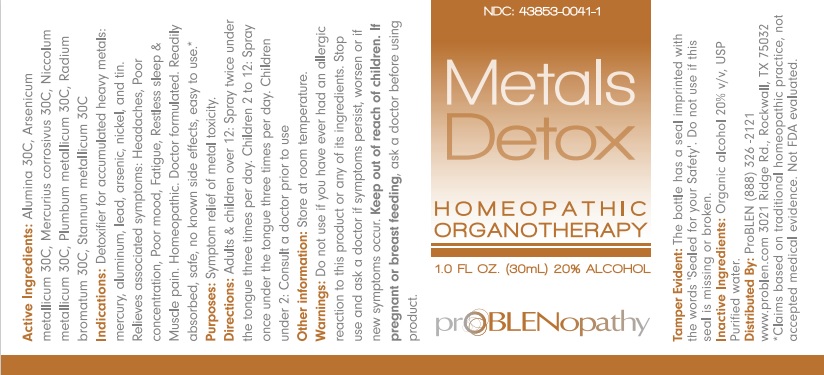 DRUG LABEL: Metals Detox
NDC: 43853-0041 | Form: LIQUID
Manufacturer: ProBLEN
Category: homeopathic | Type: HUMAN OTC DRUG LABEL
Date: 20221130

ACTIVE INGREDIENTS: ALUMINUM OXIDE 30 [hp_C]/30 mL; MERCURIC CHLORIDE 30 [hp_C]/30 mL; NICKEL 30 [hp_C]/30 mL; LEAD 30 [hp_C]/30 mL; RADIUM BROMIDE 30 [hp_C]/30 mL; TIN 30 [hp_C]/30 mL
INACTIVE INGREDIENTS: ALCOHOL; WATER

Metals Detox

ACTIVE INGREDIENT

Active Ingredients: Alumina 30C, Arsenicum metallicum 30C, Mercurius corrosivus 30C, Niccolum metallicum 30C, Plumbum metallicum 30C, Radium bromatum 30C, Stannum metallicum 30C.

*Claims based on traditional homeopathic practice, not accepted medical evidence. Not FDA evaluated.

INDICATIONS AND USAGE

Indications: Detoxifier for accumulated heavy metals: mercury, aluminum, lead, arsenic, nickel, and tin. Relieves associated symptoms: Headaches, Poor concentration, Poor mood, Fatigue, Restless sleep & Muscle pain. Homeopathic. Doctor formulated. Readily absorved, safe, no known side effects, easy to use.*

WARNINGS

Warnings: Do not use if you have ever had an allergic reaction to this product or any of its ingredients. Stop use and ask a doctor if symptoms persist, worsen or if new symptoms occur.

Keep out of reach of children. If pregnant or breast feeding, ask a doctor before using product.

DOSAGE AND ADMINISTRATION

Directions: Adults & children over 12: Spray twice under the tongue three times per day. Children 2 to 12: Spray once under the tongue three times per day. Children under 2: Consult a doctor prior to use.

Other information: Store at room temperature.

Tamper Evident: The bottle has a seal imprinted with the words "Sealed for your Safety". Do not use if this seal is missing or broken.

INACTIVE INGREDIENT

Inactive Ingredients: Organic alcohol 20% v/v, USP Purified water.

QUESTIONS

Distributed By: ProBLEN (888) 326 - 2121

www.problen.com 3021 Ridge Rd., Rockwall, TX 75032

PACKAGE LABEL

NDC: 43853-0041-1

Metals

Detox

HOMEOPATHIC

ORGANOTHERAPY

1.0 FL OZ. (30mL) 20% ALCOHOL

prOBLENopathy

PURPOSE

Purposes: Symptom relief of metal toxicity.